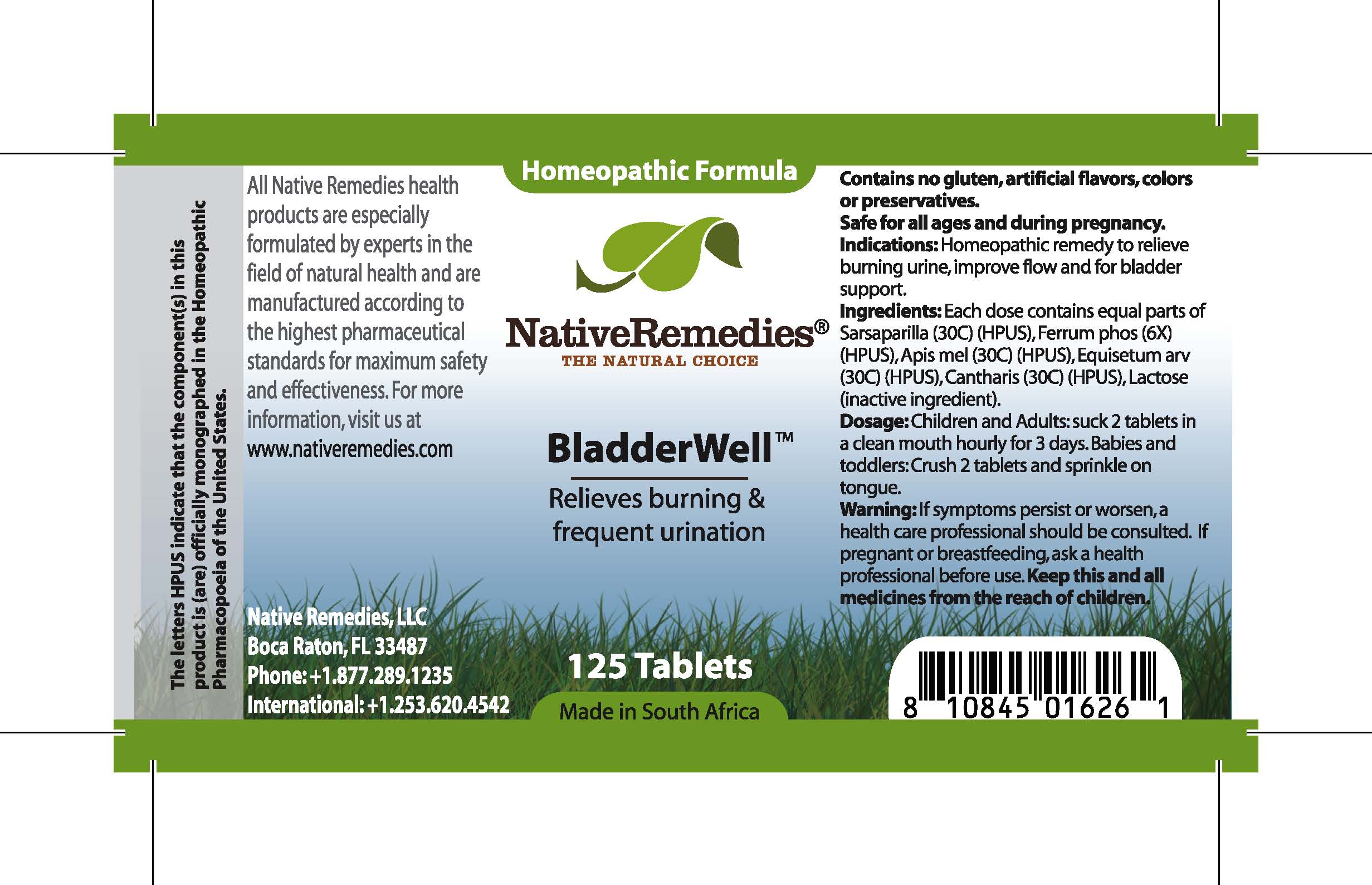 DRUG LABEL: BladderWell
								
NDC: 68647-115 | Form: TABLET
Manufacturer: Feelgood Health
Category: homeopathic | Type: HUMAN OTC DRUG LABEL
Date: 20100713

ACTIVE INGREDIENTS: SARSAPARILLA ROOT 30 [hp_C]/1 1; FERRUM PHOSPHORICUM 6 [hp_X]/1 1; APIS MELLIFERA 30 [hp_C]/1 1; EQUISETUM ARVENSE TOP 30 [hp_C]/1 1; LYTTA VESICATORIA 30 [hp_C]/1 1
INACTIVE INGREDIENTS: LACTOSE

BladderWell

INDICATIONS AND USAGE

Indications: Homeopathic remedy to relieve burning urine, improve flow and for bladder support.

DOSAGE AND ADMINISTRATION

Dosage: Children and Adults: Dissolve 2 tablets in a clean mouth hourly for 3 days. Babies and toddlers: Crush 2 tablets and sprinkle on tongue.

GENERAL PRECAUTIONS

Caution: If symptoms persist or worsen, a health care professional should be consulted.

ACTIVE INGREDIENT

Ingredients: Each dose contains equal parts of Sarsaparilla (30C) (HPUS), Ferrum phos (6X) (HPUS), Apis mel (30C) (HPUS), Equisetum arv (30C) (HPUS), Cantharis (30C) (HPUS)

Lactose (inactive ingredient).

PREGNANCY

If pregnant or breastfeeding, ask a health professional before use.

WARNINGS

Contains no gluten, artificial flavors, colors or preservatives. Safe for all ages and during pregnancy.

PATIENT COUNSELING INFORMATION

All Native Remedies health products are especially formulated by experts in the field of natural health and are manufactured according to the highest pharmaceutical standards for maximum safety and effectiveness. For more information, visit us at www.nativeremedies.com

Distributed by

Native Remedies, LLC

6531 Park of Commerce Blvd.

Suite 160

Boca Raton, FL 33487

Phone: +1.877.289.1235

International: +1.561.999.8857

The letters HPUS indicate that the component(s) in this product is (are) officially monographed in the Homeopathic Pharmacopoeia of the United States.

KEEP OUT OF REACH OF CHILDREN

Keep this and all medicines from the reach of children.

PURPOSE

Relieves burning and frequent urination